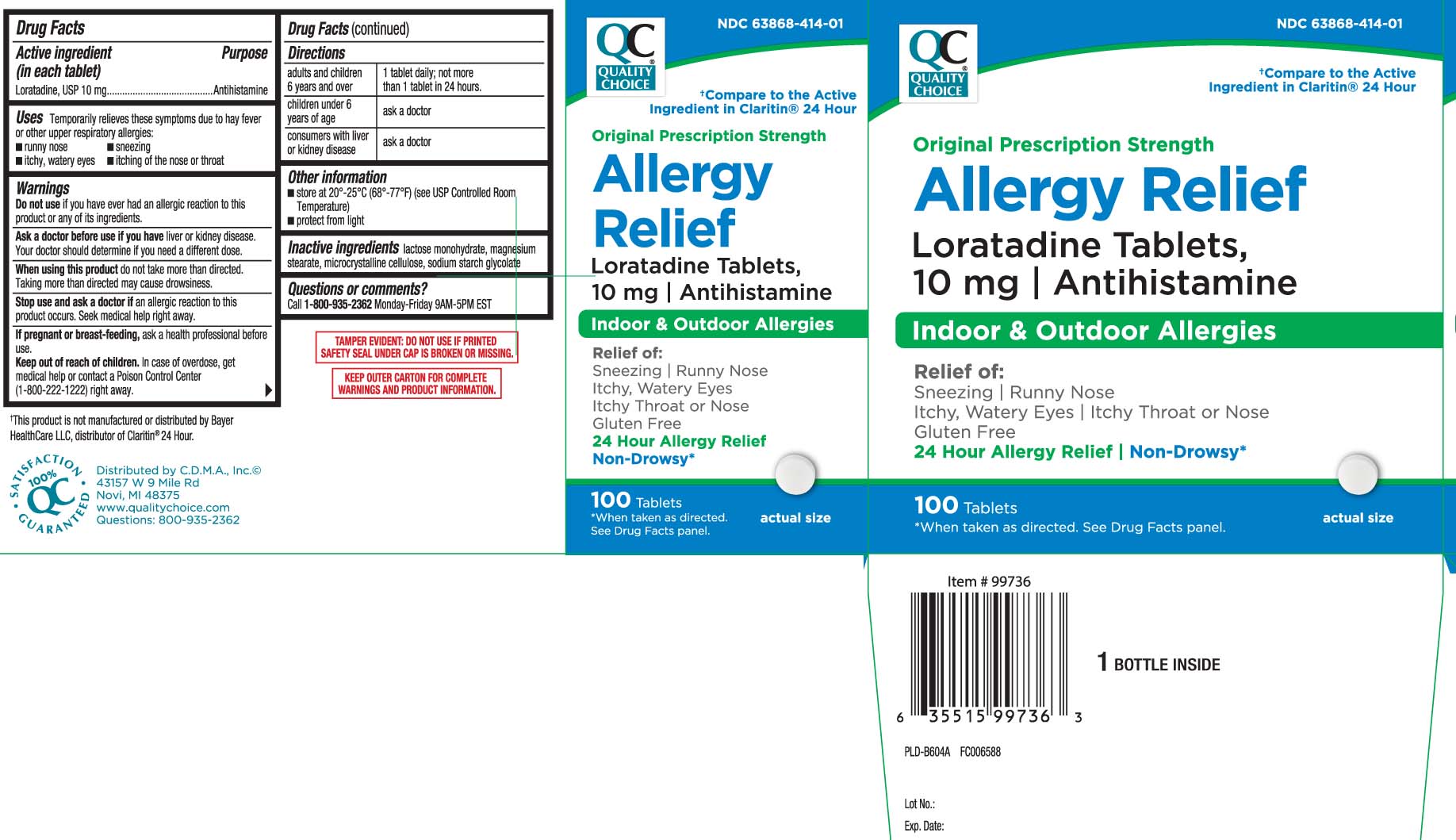 DRUG LABEL: Allergy Relief
NDC: 63868-414 | Form: TABLET
Manufacturer: QUALITY CHOICE (Chain Drug Marketing Association)
Category: otc | Type: HUMAN OTC DRUG LABEL
Date: 20251205

ACTIVE INGREDIENTS: LORATADINE 10 mg/1 1
INACTIVE INGREDIENTS: LACTOSE MONOHYDRATE; MAGNESIUM STEARATE; MICROCRYSTALLINE CELLULOSE; SODIUM STARCH GLYCOLATE TYPE A CORN

Drug Facts

Active ingredient (in each tablet)

Loratadine, USP 10 mg

Purpose

Antihistamine

Uses

temporarily relieves these symptoms due to hay fever or other upper respiratory allergies:

- runny nose
- sneezing
- itchy, watery eyes
- itching of the nose or throat

Warnings

Do not use

if you have ever had an allergic reaction to this product or any of its ingredients.

Ask a doctor before use if you have

liver or kidney disease. Your doctor should determine if you need a different dose.

When using this product,

do not take more than directed. Taking more than directed may cause drowsiness.

Stop use and ask a doctor if

an allergic reaction to this product occurs. Seek medical help right away

If pregnant or breast-feeding,

ask a health professional before use.

Keep out of reach of children.

In case of overdose, get medical help or contact a Poison Control Center (1-800-222-1222) right away.

Directions

adults and children 6 years and over | 1 tablet daily; not more than 1 tablet in 24 hours
children under 6 years of age | ask a doctor
consumers with liver or kidney disease | ask a doctor

Other information

- store at 20º-25ºC (68º-77ºF) (see UPS Controlled Room Temperature)
- protect from light

Inactive ingredients

lactose monohydrate, magnesium stearate, microcrystalline cellulose, sodium starch glycolate

Questions or comments?

Call 800-935-2362 Monday-Friday 9AM-5PM EST

Principal Display Panel

†Compare to the Active Ingredient in Claritin® 24 Hour

Original Prescription Strength

Allergy Relief

Loratadine 10 mg Tablets

Antihistamine

Indoor & Outdoor Allergies

Relief of:

Sneezing | Runny Nose

Itchy, Watery Eyes | Itchy Throat or Nose

Gluten Free

24 Hour Allergy Relief

Non-Drowsy*

Tablets

*When taken as directed. See Drug Facts panel.

†This product is not manufactured or distributed by Bayer Healthcare LLC, distributor of Claritin® 24 Hour

TAMPER EVIDENT: DO NOT USE IF PRINTED SFETY SEAL UNDER CAP IS BROKEN OR MISSING

KEEP OUTER CARTON FOR COMPLETE WARNINGS AND PRODUCT INFORMATION

Distributed by C.D.M.A., Inc.©

43157 W 9 Mile Rd

Novi, MI 48375

www.qualitychoice.com

Package Label

QUALITY CHOICE Allergy Relief